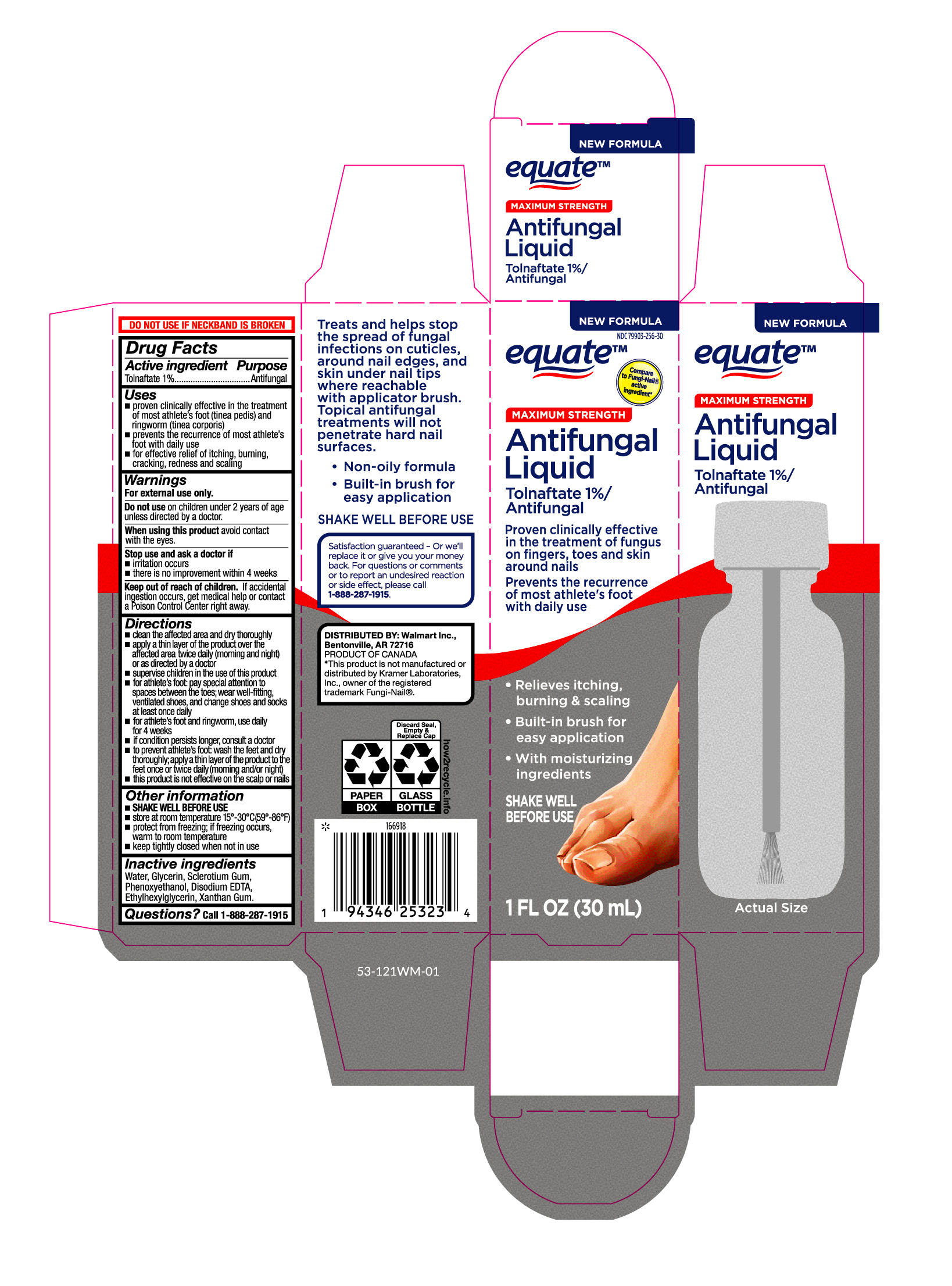 DRUG LABEL: Antifungal Liquid
NDC: 79903-256 | Form: LIQUID
Manufacturer: Wal-Mart Stores, Inc.
Category: otc | Type: HUMAN OTC DRUG LABEL
Date: 20260204

ACTIVE INGREDIENTS: TOLNAFTATE 10 mg/1 mL
INACTIVE INGREDIENTS: WATER; GLYCERIN; XANTHAN GUM; ETHYLHEXYLGLYCERIN; EDETATE DISODIUM; PHENOXYETHANOL; SCLEROTIUM GUM

Equate Antifungal Liquid

Active ingredient

Tolnaftate 1%

Purpose

Antifungal

Uses

proven clinically effective in the treatment of most athlete's foot (tinea pedis) and ringworm (tinea corporis)

prevents the recurrence of most athlete's foot with daily use

for effective relief of itching, burning, cracking, redness and scaling

Warnings

For external use only.

Do not use

on children under 2 years of age unless directed by a doctor.

When using this product

avoid contact with the eyes.

Stop use and consult a doctor if

- irritation occurs
- there is no improvement within 4 weeks

Keep out of reach of children.

If accidental ingestion occurs, get medical help or contact a Poison Control Center right away.

Directions

- clean the affected area and dry thoroughly
- apply a thin layer of the product over the affected area twice daily (morning and night) or as directed by a doctor
- supervise children in the use of this product
- for athlete's foot: pay special attention to spaces between the toes; wear well-fitting, ventilated shoes, and change shoes and socks at least once daily
- for athlete's foot and ringworm, use daily for 4 weeks.
- if condition persists longer, consult a doctor
- to prevent athlete's foot: wash the feet and dry thoroughly; apply a thin layer of the product to the feet once or twice daily (morning and/or night)
- this product is not effective on the scalp or nails

Other information

- SHAKE WELL BEFORE USE
- store at room temperature 15°-30°C (59° - 86°F)
- protect from freezing; if freezing occurs, warm to room temperature
- keep tightly closed when not in use

Inactive ingredient

WATER, GLYCERIN, SCLEROTIUM GUM, PHENOXYETHANOL, DISODIUM EDTA, ETHYLHEXYLGLYCERIN, XANTHAN GUM

Questions?

Call 1-888-287-1915

Principal Display Panel

equate

MAXIMUM STRENGTH

Antifungal

Liquid

Tolnaftate 1%/

Antifungal

Proven clinically effective

in the treatment of fungus

on fingers, toes and skin

around nails

Prevents the recurrence

of most athlete's foot

with daily use

Relieves itching,

burning & scaling

Built-in brush for

easy application

With moisturizing

ingredients

SHAKE WELL

BEFORE USE

1 FL OZ (30 mL)